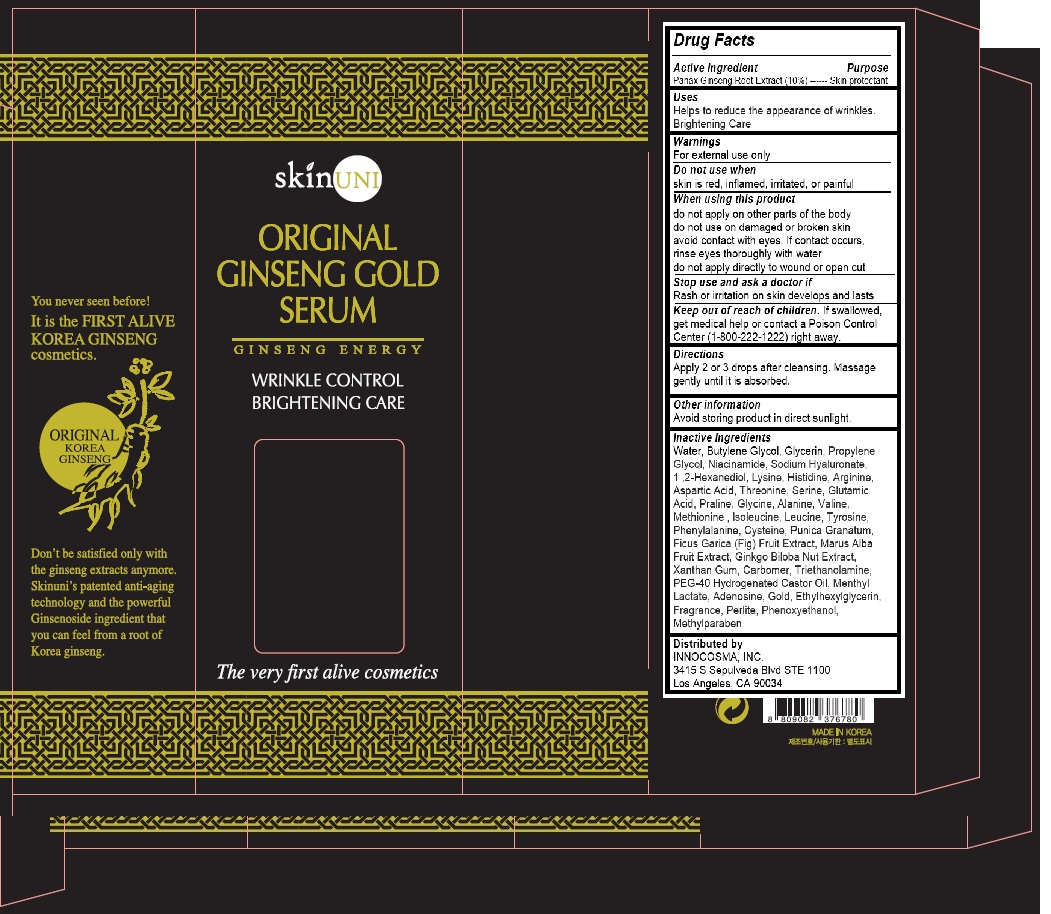 DRUG LABEL: SKINUNI Original Ginseng Gold Serum
NDC: 72555-100 | Form: EXTRACT
Manufacturer: INNOCOSMA, INC
Category: otc | Type: HUMAN OTC DRUG LABEL
Date: 20191220

ACTIVE INGREDIENTS: PANAX GINSENG ROOT WATER 10 g/100 g
INACTIVE INGREDIENTS: WATER

SKINUNI Original Ginseng Gold Serum

Directions

Apply 2 or 3 drops after cleansing. Massage gently until it is absorbed.

Warnings

For external use only

Inactive Ingredients

Water, Butylene Glycol, Glycerin, Propylene Glycol, Niacinamide, Sodium Hyaluronate, 1 ,2-Hexanediol, Lysine, Histidine, Arginine, Aspartic Acid, Threonine, Serine, Glutamic Acid, Praline, Glycine, Alanine, Valine, Methionine , lsoleucine, Leucine, Tyrosine, Phenylalanine, Cysteine, Punica Granatum, Ficus Garica (Fig) Fruit Extract, Marus Alba Fruit Extract, Ginkgo Biloba Nut Extract, Xanthan Gum, Carbomer, Triethanolamine, PEG-40 Hydrogenated Castor Oil, Menthyl Lactate, Adenosine, Gold, Ethylhexylglycerin, Fragrance, Perlite, Phenoxyethanol, Methylparaben

Uses

Helps to reduce the appearance of wrinkles.

Brightening Care

Active Ingredient

Panax Ginseng Root Extract (10%)

Purpose

Skin protectant

Keep out of reach of children.

If swallowed, get medical help or contact a Poison Control Center (1-800-222-1222) right away.